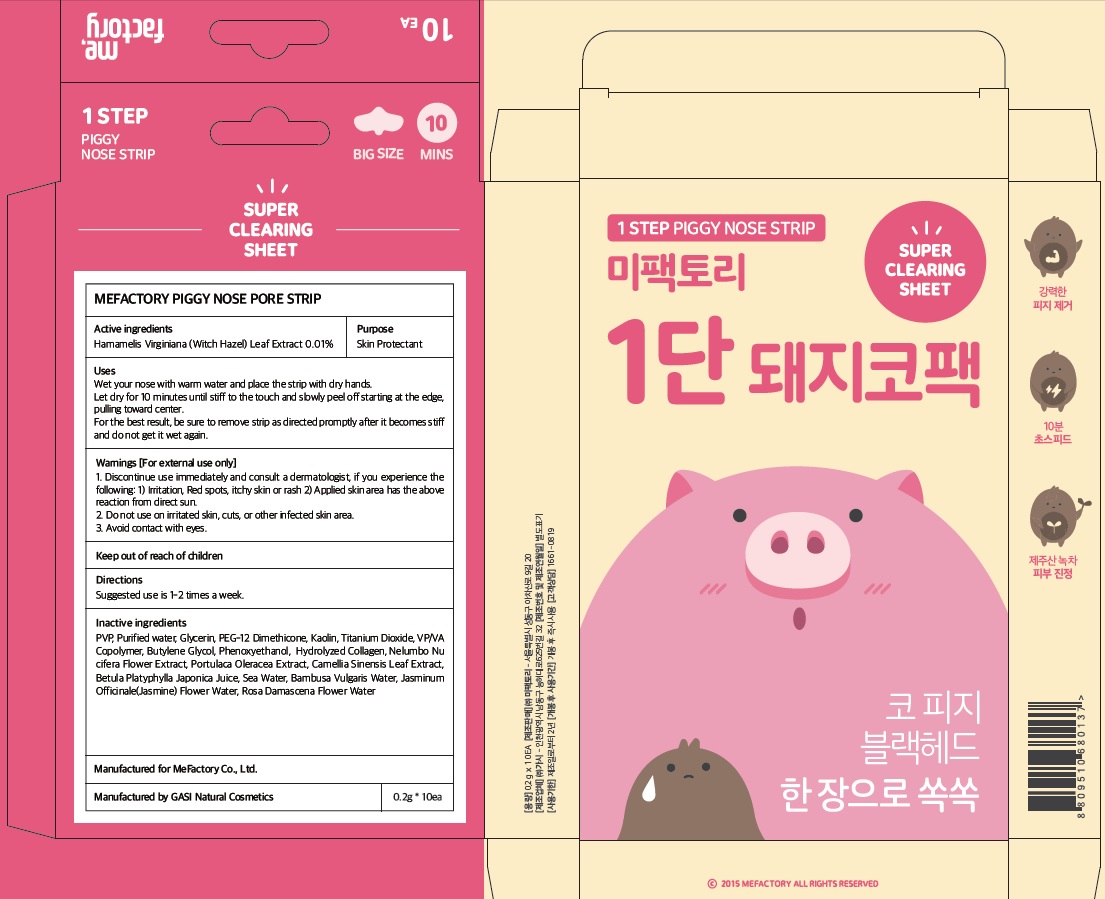 DRUG LABEL: Mefactory Piggy Nose Pore Strip
NDC: 70908-140 | Form: PATCH
Manufacturer: MeFactory Co., Ltd.
Category: otc | Type: HUMAN OTC DRUG LABEL
Date: 20170808

ACTIVE INGREDIENTS: Witch Hazel 0.02 mg/0.2 g
INACTIVE INGREDIENTS: WATER; Glycerin

ACTIVE INGREDIENT

Active ingredients: Hamamelis Virginiana (Witch Hazel) Leaf Extract 0.01%

INACTIVE INGREDIENT

Inactive ingredients: PVP, Purified water, Glycerin, PEG-12 Dimethicone, Kaolin, Titanium Dioxide, VP/VA Copolymer, Butylene Glycol, Phenoxyethanol, Hydrolyzed Collagen, Nelumbo Nucifera Flower Extract, Portulaca Oleracea Extract, Camellia Sinensis Leaf Extract, Betula Platyphylla Japonica Juice, Sea Water, Bambusa Vulgaris Water, Jasminum Officinale (Jasmine) Flower Water , Rosa Damascena Flower Water

PURPOSE

Purpose: Skin Protectant

WARNINGS

Warnings: For external use only. 1. Discontinue use immediately and consult a dermatologist, if you experience the following: 1) Irritation, Red spots, itchy skin or rash 2) Applied skin area has the above reaction from direct sun 2. Do not use on irritated skin, cuts, or other infected skin area. 3. Avoid contact with eyes.

KEEP OUT OF REACH OF CHILDREN

Uses

Uses: Wet your nose with warm water and place the strip with dry hands. Let dry for 10 minutes until stiff to the touch and slowly peel off starting at the edge, pulling toward center. For the best result, be sure to remove strip as directed promptly after it becomes stiff and do not get it wet again.

Directions

Directions: Suggested use is 1-2 times a week